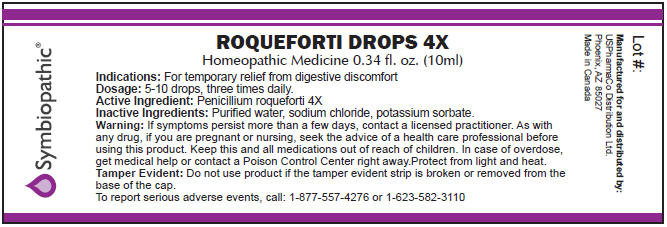 DRUG LABEL: Roqueforti
NDC: 49693-1801 | Form: LIQUID
Manufacturer: USPharmaCo
Category: homeopathic | Type: HUMAN OTC DRUG LABEL
Date: 20091223

ACTIVE INGREDIENTS: Penicillium roqueforti 4 [hp_X]/10 mL

ROQUEFORTI
DROPS 4X

Homeopathic Medicine

Indications

For temporary relief from digestive discomfort

Dosage

5-10 drops, three times daily.

Active Ingredient

Penicillium roqueforti 4X

Inactive Ingredients

Purified water, sodium chloride, potassium sorbate.

Warning

If symptoms persist more than a few days, contact a licensed practitioner. As with any drug, if you are pregnant or nursing, seek the advice of a health care professional before using this product.

KEEP OUT OF REACH OF CHILDREN

Keep this and all medications out of reach of children. In case of overdose, get medical help or contact a Poison Control Center right away.

STORAGE AND HANDLING

Protect from light and heat.

Tamper Evident

Do not use product if the tamper evident strip is broken or removed from the base of the cap.

To report serious adverse events, call: 1-877-557-4276 or 1-623-582-3110

Manufactured for and distributed by:
USPharmaCo Distribution Ltd.
2205 W. Lone Cactus Drive #19,
Phoenix, AZ 85027
www.uspharmaco.com
info@uspharmaco.com

Made in Canada

PRINCIPAL DISPLAY PANEL - 10 ml Label

ROQUEFORTI DROPS 4X

Homeopathic Medicine 0.34 fl. oz. (10ml)

Indications: For temporary relief from digestive discomfort
Dosage: 5-10 drops, three times daily.
Active Ingredient: Penicillium roqueforti 4X
Inactive Ingredients: Purified water, sodium chloride, potassium sorbate.
Warning: If symptoms persist more than a few days, contact a licensed practitioner. As with
any drug, if you are pregnant or nursing, seek the advice of a health care professional before
using this product. Keep this and all medications out of reach of children. In case of overdose,
get medical help or contact a Poison Control Center right away.Protect from light and heat.
Tamper Evident: Do not use product if the tamper evident strip is broken or removed from the
base of the cap.
To report serious adverse events, call: 1-877-557-4276 or 1-623-582-3110